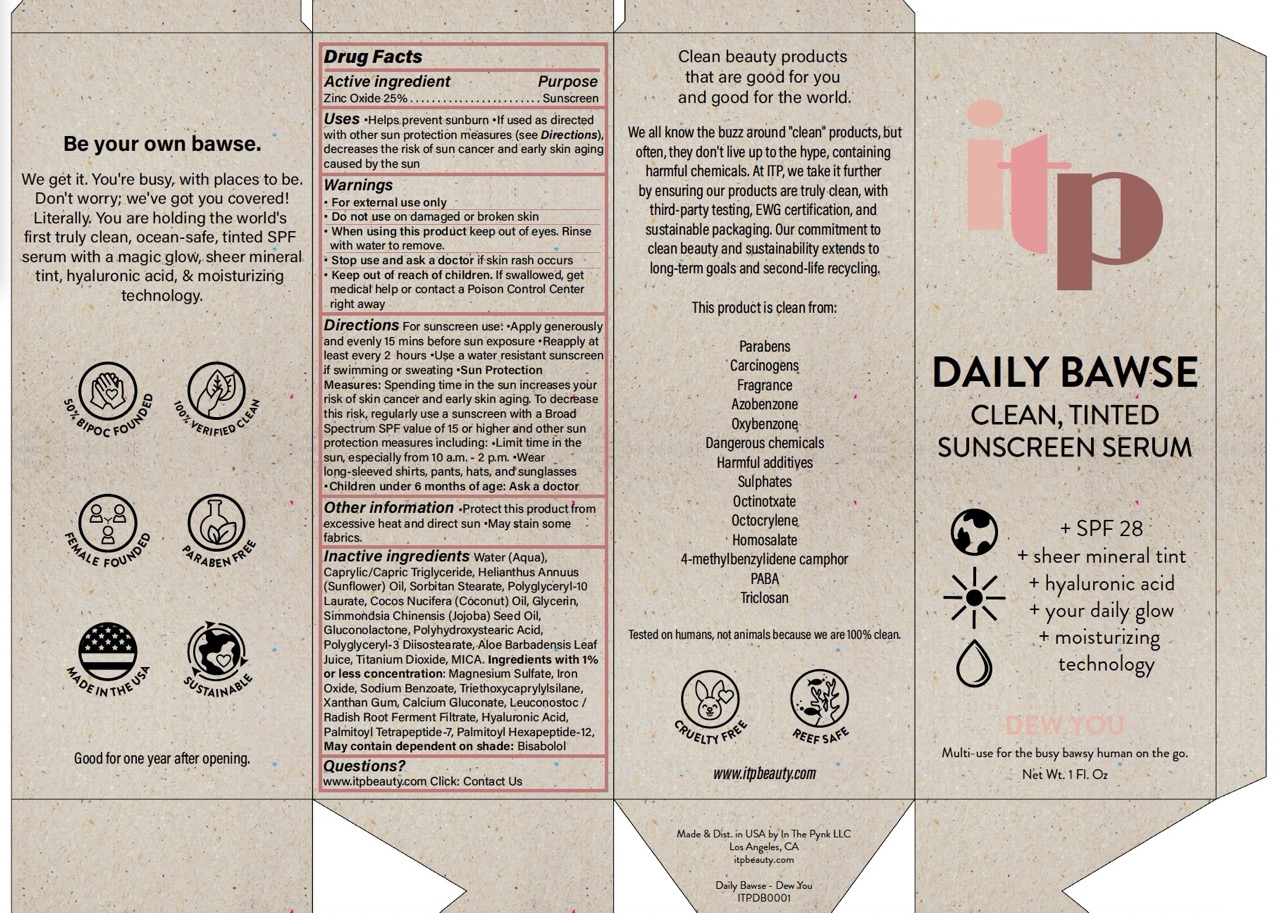 DRUG LABEL: ITP DAILY BAWSE CLEAN, TINTED SUNSCREEN SERUM SPF 28 DEW YOU
NDC: 84174-0020 | Form: LOTION
Manufacturer: In The Pynk LLC
Category: otc | Type: HUMAN OTC DRUG LABEL
Date: 20251107

ACTIVE INGREDIENTS: ZINC OXIDE 25 g/100 mL
INACTIVE INGREDIENTS: JOJOBA OIL; SUNFLOWER OIL; FERRIC OXIDE RED; COCONUT OIL; GLUCONOLACTONE; POLYHYDROXYSTEARIC ACID (2300 MW); XANTHAN GUM; POLYGLYCERYL-3 DIISOSTEARATE; ALOE VERA LEAF; LEUCONOSTOC/RADISH ROOT FERMENT FILTRATE; POLYGLYCERYL-10 LAURATE; TRIETHOXYCAPRYLYLSILANE; MICA; MAGNESIUM SULFATE, UNSPECIFIED FORM; PALMITOYL TETRAPEPTIDE-7; MEDIUM-CHAIN TRIGLYCERIDES; SODIUM BENZOATE; CALCIUM GLUCONATE; HYALURONIC ACID; WATER; SORBITAN MONOSTEARATE; GLYCERIN; TITANIUM DIOXIDE; PALMITOYL HEXAPEPTIDE-12; LEVOMENOL

ITP Daily Bawse Clean, Tinted Sunscreen Serum SPF 28 1 fl oz Dew You

Active ingredient

Zinc Oxide 25%

Purpose

Sunscreen

Uses

Helps prevent sunburn

If used as directed with other sun protection measures (see Directions), decreases the risk of sun cancer and early skin aging caused by the sun

Warnings

- For external use only

Do not use

on damaged or broken skin

When using this product

keep out of eyes. Rinse with water to remove.

Stop use and ask a doctor

if skin rash occurs

Keep out of reach of children.

If swallowed, get medical help or contact a Poison Control Center right away

Directions

For sunscreen use:

- Apply generously and evenly 15 mins before sun exposure
- Reapply at least every 2 hours
- Use a water resistant sunscreen if swimming or sweating

Sun protection measures:

Spending time in the sun increases your risk of skin cancer and early skin aging. To decrease this risk, regularly use a sunscreen with a Broad Spectrum SPF value of 15 or higher and other sun protection measures including:

- Limit time in the sun, especially from 10 a.m. - 2 p.m.
- Wear long-sleeved shirts, pants, hats, and sunglasses

Children under 6 months of age: Ask a doctor

Other information

- Protect this product from excessive heat and direct sun
- May stain some fabrics

Inactive ingredients

Water (Aqua), Caprylic/Capric Triglyceride, Helianthus Annuus (Sunflower) Seed Oil, Sorbitan Stearate, Polyglyceryl-10 Laurate, Cocos Nucifera (Coconut) Oil, Glycerin, Simmondsia Chinensis (Jojoba) Seed Oil, Gluconolactone, Polyhydroxystearic Acid, Polyglyceryl-3 Diisostearate, Aloe Barbadensis (Aloe Vera) Leaf Juice, Titanium Dioxide, Mica. Ingredients with 1% or less concentration: Magnesium Sulfate, Iron Oxide, Sodium Benzoate, Triethoxycaprylylsilane, Xanthan Gum, Calcium Gluconate, Leuconostoc / Radish Root Ferment Filtrate, Hyaluronic Acid, Palmitoyl Tetrapeptide-7, Palmitoyl Hexapeptide-12, May contain dependent on shade: Bisabolol

Questions?

www.itpbeauty.com Click: Contact Us

Principal Display Panel

ITP

DAILY BAWSE

CLEAN, TINTED

SUNSCREEN SERUM

+ SPF 28

+ sheer mineral tint

+ hyaluronic acid

+ your daily glow

+ moisturizing technology

DEW YOU

Multi-use for the busy bawsy human on the go.

Net Wt. 1 Fl. Oz